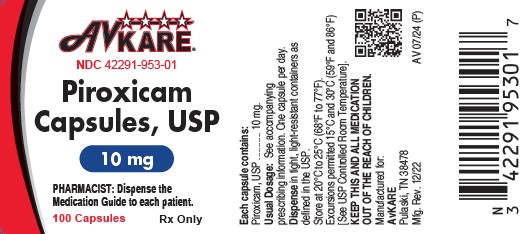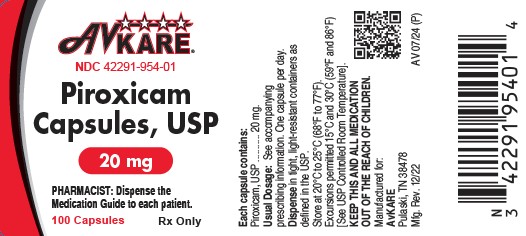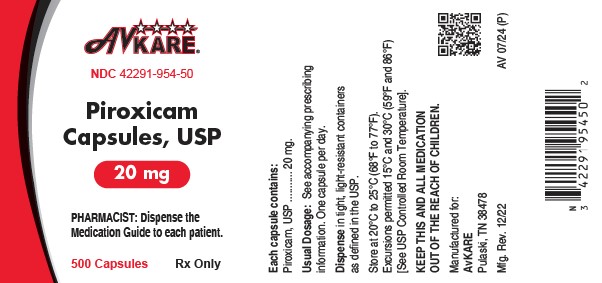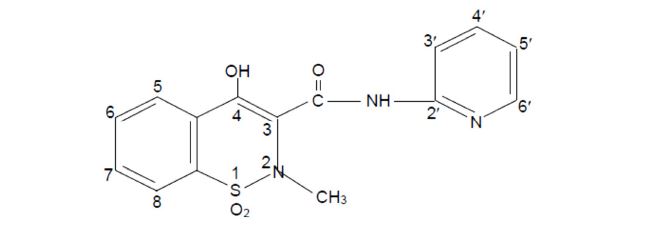 DRUG LABEL: Piroxicam
NDC: 42291-954 | Form: CAPSULE
Manufacturer: AvKARE
Category: prescription | Type: HUMAN PRESCRIPTION DRUG LABEL
Date: 20260119

ACTIVE INGREDIENTS: PIROXICAM 20 mg/1 1
INACTIVE INGREDIENTS: FD&C BLUE NO. 1; FD&C RED NO. 3; GELATIN; LACTOSE MONOHYDRATE; MAGNESIUM STEARATE; POTASSIUM HYDROXIDE; SHELLAC; SODIUM LAURYL SULFATE; STARCH, CORN; TITANIUM DIOXIDE

HIGHLIGHTS OF PRESCRIBING INFORMATION

Piroxicam Capsules, USP
Rx only
These highlights do not include all the information needed to use PIROXICAM CAPSULES safely and effectively. See full prescribing information for PIROXICAM CAPSULES.
Initial U.S. Approval: 1982

BOXED WARNING

WARNING: RISK OF SERIOUS CARDIOVASCULAR AND GASTROINTESTINAL EVENTS

See full prescribing information for complete boxed warning.

- Nonsteroidal anti-inflammatory drugs (NSAIDs) cause an increased risk of serious cardiovascular thrombotic events, including myocardial infarction and stroke, which can be fatal. This risk may occur early in treatment and may increase with duration of use (5.1)
- Piroxicam Capsules are contraindicated in the setting of coronary artery bypass graft (CABG) surgery (4, 5.1)
- NSAIDs cause an increased risk of serious gastrointestinal (GI) adverse events including bleeding, ulceration, and perforation of the stomach or intestines, which can be fatal. These events can occur at any time during use and without warning symptoms. Elderly patients and patients with a prior history of peptic ulcer disease and/or GI bleeding are at greater risk for serious GI events (5.2)

1 INDICATIONS AND USAGE

Piroxicam Capsules are a nonsteroidal anti-inflammatory drug indicated for

- Relief of the signs and symptoms of osteoarthritis (OA) (1)
- Relief of the signs and symptoms of rheumatoid arthritis (RA) (1)

2 DOSAGE AND ADMINISTRATION

- Use the lowest effective dosage for shortest duration consistent with individual patient treatment goals (2)
- OA and RA: 20 mg once daily (2)

3 DOSAGE FORMS AND STRENGTHS

Piroxicam Capsules USP: 10 mg and 20 mg

4 CONTRAINDICATIONS

- Known hypersensitivity to piroxicam or any components of the drug product (4)
- History of asthma, urticaria, or other allergic-type reactions after taking aspirin or other NSAIDs (4)
- In the setting of CABG surgery (4)

5 WARNINGS AND PRECAUTIONS

- Hepatotoxicity: Inform patients of warning signs and symptoms of hepatotoxicity. Discontinue if abnormal liver tests persist or worsen or if clinical signs and symptoms of liver disease develop (5.3)
- Hypertension:Patients taking some antihypertensive medications may have impaired response to these therapies when taking NSAIDs. Monitor blood pressure (5.4, 7)
- Heart Failure and Edema: Avoid use of Piroxicam Capsules in patients with severe heart failure unless benefits are expected to outweigh risk of worsening heart failure (5.5)
- Renal Toxicity: Monitor renal function in patients with renal or hepatic impairment, heart failure, dehydration, or hypovolemia. Avoid use of Piroxicam Capsules in patients with advanced renal disease unless benefits are expected to outweigh risk of worsening renal function (5.6)
- Anaphylactic Reactions: Seek emergency help if an anaphylactic reaction occurs (5.7)
- Exacerbation of Asthma Related to Aspirin Sensitivity: Piroxicam Capsules are contraindicated in patients with aspirin-sensitive asthma. Monitor patients with preexisting asthma (without aspirin sensitivity) (5.8)
- Serious Skin Reactions: Discontinue Piroxicam Capsules at first appearance of skin rash or other signs of hypersensitivity (5.9)
- Drug Reaction with Eosinophilia and Systemic Symptoms (DRESS): Discontinue and evaluate clinically (5.10)
- Fetal Toxicity: Limit use of NSAIDs, including Piroxicam Capsules, between about 20 to 30 weeks in pregnancy due to the risk of oligohydramnios/fetal renal dysfunction. Avoid use of NSAIDs in women at about 30 weeks gestation and later in pregnancy due to the risks of oligohydramnios/fetal renal dysfunction and premature closure of the fetal ductus arteriosus (5.11, 8.1)
- Hematologic Toxicity: Monitor hemoglobin or hematocrit in patients with any signs or symptoms of anemia (5.12, 7)

6 ADVERSE REACTIONS

Most common adverse reactions (incidence >2% from clinical trials) are: nausea, constipation, flatulence, abdominal pain, diarrhea, headache, dizziness, edema, rash. (6.1)

To report SUSPECTED ADVERSE REACTIONS, contact AvKARE at 1-855-361-3993 or FDA at 1-800-FDA-1088 or www.fda.gov/medwatch.

7 DRUG INTERACTIONS

- Drugs that Interfere with Hemostasis (e.g. warfarin, aspirin, selective serotonin reuptake inhibitors [SSRIs]/serotonin norepinephrine reuptake inhibitors [SNRIs]): Monitor patients for bleeding who are concomitantly taking Piroxicam Capsules with drugs that interfere with hemostasis. Concomitant use of Piroxicam Capsules and analgesic doses of aspirin is not generally recommended (7)
- Angiotensin Converting Enzyme (ACE) Inhibitors, Angiotensin Receptor Blockers (ARB), or Beta-Blockers: Concomitant use with Piroxicam Capsules may diminish the antihypertensive effect of these drugs. Monitor blood pressure (7)
- ACE Inhibitors and ARBs: Concomitant use with Piroxicam Capsules in elderly, volume depleted, or those with renal impairment may result in deterioration of renal function. In such high risk patients, monitor for signs of worsening renal function (7)
- Diuretics: NSAIDs can reduce natriuretic effect of furosemide and thiazide diuretics. Monitor patients to assure diuretic efficacy including antihypertensive effects (7)
- Digoxin: Concomitant use of Piroxicam Capsules can increase serum concentration and prolong half-life of digoxin. Monitor serum digoxin levels (7)

8 USE IN SPECIFIC POPULATIONS

Infertility: NSAIDs are associated with reversible infertility. Consider withdrawal of Piroxicam Capsules in women who have difficulties conceiving (8.3)

FULL PRESCRIBING INFORMATION

BOXED WARNING

WARNING: RISK OF SERIOUS CARDIOVASCULAR AND GASTROINTESTINAL EVENTS

Cardiovascular Thrombotic Events

- Nonsteroidal anti-inflammatory drugs (NSAIDs) cause an increased risk of serious cardiovascular thrombotic events, including myocardial infarction and stroke, which can be fatal. This risk may occur early in treatment and may increase with duration of use [see Warnings and Precautions (5.1)].
- Piroxicam Capsules are contraindicated in the setting of coronary artery bypass graft (CABG) surgery [see Contraindications (4) and Warnings and Precautions (5.1)].

Gastrointestinal Bleeding, Ulceration, and Perforation

- NSAIDs cause an increased risk of serious gastrointestinal (GI) adverse events including bleeding, ulceration, and perforation of the stomach or intestines, which can be fatal. These events can occur at any time during use and without warning symptoms. Elderly patients and patients with a prior history of peptic ulcer disease and/or GI bleeding are at greater risk for serious GI events [see Warnings and Precautions (5.2)].

1 INDICATIONS AND USAGE

Piroxicam Capsules are indicated:

- For relief of the signs and symptoms of osteoarthritis.
- For relief of the signs and symptoms of rheumatoid arthritis.

2 DOSAGE AND ADMINISTRATION

Carefully consider the potential benefits and risks of Piroxicam Capsules and other treatment options before deciding to use Piroxicam Capsules. Use the lowest effective dosage for the shortest duration consistent with individual patient treatment goals [see Warnings and Precautions (5)].

After observing the response to initial therapy with Piroxicam Capsules, the dose and frequency should be adjusted to suit an individual patient's needs.

For the relief of rheumatoid arthritis and osteoarthritis, the dosage is 20 mg given orally once per day. If desired, the daily dose may be divided. Because of the long half-life of Piroxicam Capsules, steady-state blood levels are not reached for 7 to 12 days. Therefore, although the therapeutic effects of Piroxicam Capsules are evident early in treatment, there is a progressive increase in response over several weeks and the effect of therapy should not be assessed for two weeks.

3 DOSAGE FORMS AND STRENGTHS

Piroxicam Capsules, USP:

- 10 mg are maroon opaque cap and blue opaque body imprinted with 'P10' on body
- 20 mg are maroon opaque cap and maroon opaque body imprinted with "P20" on body.

4 CONTRAINDICATIONS

Piroxicam Capsules are contraindicated in the following patients:

- Known hypersensitivity (e.g., anaphylactic reactions and serious skin reactions) to piroxicam or any components of the drug product [see Warnings and Precautions (5.7, 5.9)]
- History of asthma, urticaria, or other allergic-type reactions after taking aspirin or other NSAIDs. Severe, sometimes fatal, anaphylactic reactions to NSAIDs have been reported in such patients [see Warnings and Precautions (5.7, 5.8)]
- In the setting of CABG surgery [see Warnings and Precautions (5.1)]

5 WARNINGS AND PRECAUTIONS

5.1 Cardiovascular Thrombotic Events

Clinical trials of several cyclooxygenase-2 (COX-2) selective and nonselective NSAIDs of up to three years duration have shown an increased risk of serious cardiovascular (CV) thrombotic events, including myocardial infarction (MI), and stroke, which can be fatal. Based on available data, it is unclear that the risk for CV thrombotic events is similar for all NSAIDs. The relative increase in serious CV thrombotic events over baseline conferred by NSAID use appears to be similar in those with and without known CV disease or risk factors for CV disease. However, patients with known CV disease or risk factors had a higher absolute incidence of excess serious CV thrombotic events, due to their increased baseline rate. Some observational studies found that this increased risk of serious CV thrombotic events began as early as the first weeks of treatment. The increase in CV thrombotic risk has been observed most consistently at higher doses.

To minimize the potential risk for an adverse CV event in NSAID-treated patients, use the lowest effective dose for the shortest duration possible. Physicians and patients should remain alert for the development of such events, throughout the entire treatment course, even in the absence of previous CV symptoms. Patients should be informed about the symptoms of serious CV events and the steps to take if they occur.

There is no consistent evidence that concurrent use of aspirin mitigates the increased risk of serious CV thrombotic events associated with NSAID use. The concurrent use of aspirin and an NSAID, such as piroxicam, increases the risk of serious gastrointestinal (GI) events [see Warnings and Precautions (5.2)].

Status Post Coronary Artery Bypass Graft (CABG) Surgery

Two large, controlled clinical trials of a COX-2 selective NSAID for the treatment of pain in the first 10 to 14 days following CABG surgery found an increased incidence of myocardial infarction and stroke. NSAIDs are contraindicated in the setting of CABG [see Contraindications (4)].

Post-MI Patients

Observational studies conducted in the Danish National Registry have demonstrated that patients treated with NSAIDs in the post-MI period were at increased risk of reinfarction, CV-related death, and all-cause mortality beginning in the first week of treatment. In this same cohort, the incidence of death in the first year post-MI was 20 per 100 person years in NSAID-treated patients compared to 12 per 100 person years in non-NSAID exposed patients. Although the absolute rate of death declined somewhat after the first year post-MI, the increased relative risk of death in NSAID users persisted over at least the next four years of follow-up.

Avoid the use of Piroxicam Capsules in patients with a recent MI unless the benefits are expected to outweigh the risk of recurrent CV thrombotic events. If Piroxicam Capsules are used in patients with a recent MI, monitor patients for signs of cardiac ischemia.

5.2 Gastrointestinal Bleeding, Ulceration, and Perforation

NSAIDs, including piroxicam capsules, cause serious gastrointestinal (GI) adverse events including inflammation, bleeding, ulceration, and perforation of the esophagus, stomach, small intestine, or large intestine, which can be fatal. These serious adverse events can occur at any time, with or without warning symptoms, in patients treated with NSAIDs. Only one in five patients who develop a serious upper GI adverse event on NSAID therapy is symptomatic. Upper GI ulcers, gross bleeding, or perforation caused by NSAIDs occurred in approximately 1% of patients treated for 3 to 6 months, and in about 2% to 4% of patients treated for one year. However, even short-term NSAID therapy is not without risk.

Risk Factors for GI Bleeding, Ulceration, and Perforation

Patients with a prior history of peptic ulcer disease and/or GI bleeding who used NSAIDs had a greater than 10-fold increased risk for developing a GI bleed compared to patients without these risk factors. Other factors that increase the risk of GI bleeding in patients treated with NSAIDs include longer duration of NSAID therapy; concomitant use of oral corticosteroids, antiplatelet drugs (such as aspirin), anticoagulants, or selective serotonin reuptake inhibitors (SSRIs); smoking; use of alcohol; older age; and poor general health status. Most postmarketing reports of fatal GI events occurred in elderly or debilitated patients. Additionally, patients with advanced liver disease and/or coagulopathy are at increased risk for GI bleeding.

Strategies to Minimize the GI Risks in NSAID-Treated Patients:

- Use the lowest effective dosage for the shortest possible duration.
- Avoid administration of more than one NSAID at a time.
- Avoid use in patients at higher risk unless benefits are expected to outweigh the increased risk of bleeding. For such patients, as well as those with active GI bleeding, consider alternate therapies other than NSAIDs.
- Remain alert for signs and symptoms of GI ulceration and bleeding during NSAID therapy.
- If a serious GI adverse event is suspected, promptly initiate evaluation and treatment, and discontinue Piroxicam Capsules until a serious GI adverse event is ruled out.
- In the setting of concomitant use of low-dose aspirin for cardiac prophylaxis, monitor patients more closely for evidence of GI bleeding [see Drug Interactions (7)].

5.3 Hepatotoxicity

Elevations of alanine aminotransferase (ALT) or aspartate aminotransferase (AST) (three or more times the upper limit of normal [ULN]) have been reported in approximately 1% of NSAID-treated patients in clinical trials. In addition, rare, sometimes fatal, cases of severe hepatic injury, including fulminant hepatitis, liver necrosis, and hepatic failure have been reported.

Elevations of ALT or AST (less than three times ULN) may occur in up to 15% of patients treated with NSAIDs including piroxicam.

Inform patients of the warning signs and symptoms of hepatotoxicity (e.g., nausea, fatigue, lethargy, diarrhea, pruritus, jaundice, right upper quadrant tenderness, and "flu-like" symptoms). If clinical signs and symptoms consistent with liver disease develop, or if systemic manifestations occur (e.g., eosinophilia, rash), discontinue Piroxicam Capsules immediately, and perform a clinical evaluation of the patient.

5.4 Hypertension

NSAIDs, including Piroxicam Capsules, can lead to new onset of hypertension or worsening of preexisting hypertension, either of which may contribute to the increased incidence of CV events. Patients taking angiotensin converting enzyme (ACE) inhibitors, thiazide diuretics, or loop diuretics may have impaired response to these therapies when taking NSAIDs [see Drug Interactions.(7)].

Monitor blood pressure (BP) during the initiation of NSAID treatment and throughout the course of therapy.

5.5 Heart Failure and Edema

The Coxib and traditional NSAID Trialists' Collaboration meta-analysis of randomized controlled trials demonstrated an approximately two-fold increase in hospitalizations for heart failure in COX-2 selective-treated patients and nonselective NSAID-treated patients compared to placebo-treated patients. In a Danish National Registry study of patients with heart failure, NSAID use increased the risk of MI, hospitalization for heart failure, and death.

Additionally, fluid retention and edema have been observed in some patients treated with NSAIDs. Use of piroxicam may blunt the CV effects of several therapeutic agents used to treat these medical conditions (e.g., diuretics, ACE inhibitors, or angiotensin receptor blockers [ARBs]) [see Drug Interactions (7)].

Avoid the use of Piroxicam Capsules in patients with severe heart failure unless the benefits are expected to outweigh the risk of worsening heart failure. If Piroxicam Capsules are used in patients with severe heart failure, monitor patients for signs of worsening heart failure.

5.6 Renal Toxicity and Hyperkalemia

Renal Toxicity

Long-term administration of NSAIDs has resulted in renal papillary necrosis and other renal injury.

Renal toxicity has also been seen in patients in whom renal prostaglandins have a compensatory role in the maintenance of renal perfusion. In these patients, administration of an NSAID may cause a dose-dependent reduction in prostaglandin formation and, secondarily, in renal blood flow, which may precipitate overt renal decompensation. Patients at greatest risk of this reaction are those with impaired renal function, dehydration, hypovolemia, heart failure, liver dysfunction, those taking diuretics and ACE inhibitors or ARBs, and the elderly. Discontinuation of NSAID therapy is usually followed by recovery to the pretreatment state.

No information is available from controlled clinical studies regarding the use of Piroxicam Capsules in patients with advanced renal disease. The renal effects of Piroxicam Capsules may hasten the progression of renal dysfunction in patients with preexisting renal disease.

Correct volume status in dehydrated or hypovolemic patients prior to initiating Piroxicam Capsules. Monitor renal function in patients with renal or hepatic impairment, heart failure, dehydration, or hypovolemia during use of Piroxicam Capsules [see Drug Interactions (7)]. Avoid the use of Piroxicam Capsules in patients with advanced renal disease unless the benefits are expected to outweigh the risk of worsening renal function. If Piroxicam Capsules are used in patients with advanced renal disease, monitor patients for signs of worsening renal function.

Hyperkalemia

Increases in serum potassium concentration, including hyperkalemia, have been reported with use of NSAIDs, even in some patients without renal impairment. In patients with normal renal function, these effects have been attributed to a hyporeninemic-hypoaldosteronism state.

5.7 Anaphylactic Reactions

Piroxicam has been associated with anaphylactic reactions in patients with and without known hypersensitivity to piroxicam and in patients with aspirin-sensitive asthma [see Contraindications (4) and Warnings and Precautions (5.8)].

Seek emergency help if an anaphylactic reaction occurs.

5.8 Exacerbation of Asthma Related to Aspirin Sensitivity

A subpopulation of patients with asthma may have aspirin-sensitive asthma which may include chronic rhinosinusitis complicated by nasal polyps; severe, potentially fatal bronchospasm; and/or intolerance to aspirin and other NSAIDs. Because cross-reactivity between aspirin and other NSAIDs has been reported in such aspirin-sensitive patients, Piroxicam Capsules are contraindicated in patients with this form of aspirin sensitivity [see Contraindications (4)].When Piroxicam Capsules are used in patients with preexisting asthma (without known aspirin sensitivity), monitor patients for changes in the signs and symptoms of asthma.

5.9 Serious Skin Reactions

NSAIDs, including piroxicam, can cause serious skin adverse reactions such as exfoliative dermatitis, Stevens-Johnson Syndrome (SJS), and toxic epidermal necrolysis (TEN), which can be fatal. These serious events may occur without warning. Inform patients about the signs and symptoms of serious skin reactions, and to discontinue the use of Piroxicam Capsules at the first appearance of skin rash or any other sign of hypersensitivity. Piroxicam Capsules are contraindicated in patients with previous serious skin reactions to NSAIDs [see Contraindications (4)].

5.10 Drug Reaction with Eosinophilia and Systemic Symptoms (DRESS)

Drug Reaction with Eosinophilia and Systemic Symptoms (DRESS) has been reported in patients taking NSAIDs such as Piroxicam Capsules. Some of these events have been fatal or life-threatening. DRESS typically, although not exclusively, presents with fever, rash, lymphadenopathy, and/or facial swelling. Other clinical manifestations may include hepatitis, nephritis, hematological abnormalities, myocarditis, or myositis. Sometimes symptoms of DRESS may resemble an acute viral infection. Eosinophilia is often present. Because this disorder is variable in its presentation, other organ systems not noted here may be involved. It is important to note that early manifestations of hypersensitivity, such as fever or lymphadenopathy, may be present even though rash is not evident. If such signs or symptoms are present, discontinue Piroxicam Capsules and evaluate the patient immediately.

5.11 Fetal Toxicity

Premature Closure of Fetal Ductus Arteriosus

Avoid use of NSAIDs, including Piroxicam Capsules, in pregnant women at about 30 weeks gestation and later. NSAIDs, including Piroxicam Capsules, increase the risk of premature closure of the fetal ductus arteriosus at approximately this gestational age.

Oligohydramnios/Neonatal Renal Impairment

Use of NSAIDs, including Piroxicam Capsules, at about 20 weeks gestation or later in pregnancy may cause fetal renal dysfunction leading to oligohydramnios and, in some cases, neonatal renal impairment. These adverse outcomes are seen, on average, after days to weeks of treatment, although oligohydramnios has been infrequently reported as soon as 48 hours after NSAID initiation. Oligohydramnios is often, but not always, reversible with treatment discontinuation. Complications of prolonged oligohydramnios may, for example, include limb contractures and delayed lung maturation. In some postmarketing cases of impaired neonatal renal function, invasive procedures such as exchange transfusion or dialysis were required.

If NSAID treatment is necessary between about 20 weeks and 30 weeks gestation, limit Piroxicam Capsules use to the lowest effective dose and shortest duration possible. Consider ultrasound monitoring of amniotic fluid if Piroxicam Capsules treatment extends beyond 48 hours. Discontinue Piroxicam Capsules if oligohydramnios occurs and follow up according to clinical practice [see Use in Specific Populations (8.1)].

5.12 Hematologic Toxicity

Anemia has occurred in NSAID-treated patients. This may be due to occult or gross blood loss, fluid retention, or an incompletely described effect on erythropoiesis. If a patient treated with Piroxicam Capsules has any signs or symptoms of anemia, monitor hemoglobin or hematocrit.

NSAIDs, including Piroxicam Capsules, may increase the risk of bleeding events. Co-morbid conditions such as coagulation disorders, concomitant use of warfarin, other anticoagulants, antiplatelet drugs (e.g., aspirin), SSRIs, and serotonin norepinephrine reuptake inhibitors (SNRIs) may increase this risk. Monitor these patients for signs of bleeding [see Drug Interactions (7)].

5.13 Masking of Inflammation and Fever

The pharmacological activity of Piroxicam Capsules in reducing inflammation, and possibly fever, may diminish the utility of diagnostic signs in detecting infections.

5.14 Laboratory Monitoring

Because serious GI bleeding, hepatotoxicity, and renal injury can occur without warning symptoms or signs, consider monitoring patients on long-term NSAID treatment with a complete blood count (CBC) and a chemistry profile periodically [see Warnings and Precautions (5.2, 5.3, 5.6)].

5.15 Ophthalmologic Effects

Because of reports of adverse eye findings with nonsteroidal anti-inflammatory agents, it is recommended that patients who develop visual complaints during treatment with Piroxicam Capsules have ophthalmic evaluations.

6 ADVERSE REACTIONS

The following adverse reactions are discussed in greater detail in other sections of the labeling:

- Cardiovascular Thrombotic Events [see Warnings and Precautions (5.1)]
- GI Bleeding, Ulceration and Perforation [see Warnings and Precautions (5.2)]
- Hepatotoxicity [see Warnings and Precautions (5.3)]
- Hypertension [see Warnings and Precautions (5.4)]
- Heart Failure and Edema [see Warnings and Precautions (5.5)]
- Renal Toxicity and Hyperkalemia [see Warnings and Precautions (5.6)]
- Anaphylactic Reactions [see Warnings and Precautions (5.7)]
- Serious Skin Reactions [see Warnings and Precautions (5.9)]
- Hematologic Toxicity [see Warnings and Precautions (5.12)]

6.1 Clinical Trials Experience

Because clinical trials are conducted under widely varying conditions, adverse reaction rates observed in the clinical trials of a drug cannot be directly compared to rates in the clinical trials of another drug and may not reflect the rates observed in practice.

In patients taking Piroxicam Capsules or other NSAIDs, the most frequently reported adverse experiences occurring in approximately 1% to 10% of patients are:

Cardiovascular System:Edema

Digestive System:Anorexia, abdominal pain, constipation, diarrhea, flatulence, nausea, vomiting

Nervous System:Dizziness, headache, vertigo

Skin and Appendages:Pruritus, rash

Special Senses:Tinnitus

Additional adverse experiences reported occasionally include:

Cardiovascular System:Palpitations

Digestive System:Stomatitis

Nervous System:Drowsiness

Special Senses:Blurred vision

6.2 Postmarketing Experience

The following adverse reactions have been identified during post approval use of Piroxicam Capsules. Because these reactions are reported voluntarily from a population of uncertain size, it is not always possible to reliably estimate their frequency or establish a causal relationship to drug exposure.

Body as a Whole: Fever, infection, sepsis, anaphylactic reactions, appetite changes, death, flu-like syndrome, pain (colic), serum sickness

Cardiovascular System:Congestive heart failure, hypertension, tachycardia, syncope, arrhythmia, exacerbation of angina, hypotension, myocardial infarction, vasculitis

Digestive System:Dyspepsia, elevated liver enzymes, gross bleeding/perforation, heartburn, ulcers (gastric/duodenal), dry mouth, esophagitis, gastritis, glossitis, hematemesis, hepatitis, jaundice, melena, rectal bleeding, eructation, liver failure, pancreatitis

Hemic and Lymphatic System:Anemia, increased bleeding time, ecchymosis, eosinophilia, epistaxis, leukopenia, purpura, petechial rash, thrombocytopenia, agranulocytosis, hemolytic anemia, aplastic anemia, lymphadenopathy, pancytopenia

Hypersensitivity:Positive ANA

Metabolic and Nutritional:Weight changes, Fluid retention, hyperglycemia, hypoglycemia

Nervous System:Anxiety, asthenia, confusion, depression, dream abnormalities, insomnia, malaise, nervousness, paresthesia, somnolence, tremors, akathisia, convulsions, coma, hallucinations, meningitis, mood alterations

Respiratory System:Asthma, dyspnea, respiratory depression, pneumonia

Skin and Appendages:Alopecia, bruising, desquamation, erythema, photosensitivity, sweat, angioedema, toxic epidermal necrosis, erythema multiforme, exfoliative dermatitis, onycholysis, Stevens Johnson Syndrome, urticaria, vesiculobullous reaction

Special Senses:Conjunctivitis, hearing impairment, swollen eyes

Urogenital System:Abnormal renal function, cystitis, dysuria, hematuria, hyperkalemia, interstitial nephritis, nephrotic syndrome, oliguria/polyuria, proteinuria, renal failure, glomerulonephritis

Reproductive System and Breast Disorders:Female fertility decreased

To report SUSPECTED ADVERSE REACTIONS, contact AvKARE at 1-855-361-3993 or FDA at 1-800-FDA-1088 or www.fda.gov/medwatch.

7 DRUG INTERACTIONS

See Table 1 for clinically significant drug interactions with piroxicam.

Table 1: Clinically Significant Drug Interactions with Piroxicam
Drugs That Interfere with Hemostasis
Clinical Impact: | • Piroxicam and anticoagulants such as warfarin have a synergistic effect on bleeding. The concomitant use of piroxicam and anticoagulants have an increased risk of serious bleeding compared to the use of either drug alone. • Serotonin release by platelets plays an important role in hemostasis. Case-control and cohort epidemiological studies showed that concomitant use of drugs that interfere with serotonin reuptake and an NSAID may potentiate the risk of bleeding more than an NSAID alone.
Intervention: | Monitor patients with concomitant use of Piroxicam Capsules with anticoagulants (e.g., warfarin), antiplatelet drugs (e.g., aspirin), SSRIs, and SNRIs for signs of bleeding [see Warnings and Precautions (5.12)].
Aspirin
Clinical Impact: | Controlled clinical studies showed that the concomitant use of NSAIDs and analgesic doses of aspirin does not produce any greater therapeutic effect than the use of NSAIDs alone. In a clinical study, the concomitant use of an NSAID and aspirin was associated with a significantly increased incidence of GI adverse reactions as compared to use of the NSAID alone [see Warnings and Precautions (5.2)].
Intervention: | Concomitant use of Piroxicam Capsules and analgesic doses of aspirin is not generally recommended because of the increased risk of bleeding [see Warnings and Precautions (5.12)]. Piroxicam Capsules are not a substitute for low dose aspirin for cardiovascular protection.
ACE Inhibitors, Angiotensin Receptor Blockers, and Beta-Blockers
Clinical Impact: | • NSAIDs may diminish the antihypertensive effect of ACE inhibitors, ARBs, or beta-blockers (including propranolol). • In patients who are elderly, volume-depleted (including those on diuretic therapy), or have renal impairment, co-administration of an NSAID with ACE inhibitors or ARBs may result in deterioration of renal function, including possible acute renal failure. These effects are usually reversible.
Intervention: | • During concomitant use of Piroxicam Capsules and ACE inhibitors, ARBs, or beta-blockers, monitor blood pressure to ensure that the desired blood pressure is obtained. • During concomitant use of Piroxicam Capsules and ACE inhibitors or ARBs in patients who are elderly, volume-depleted, or have impaired renal function, monitor for signs of worsening renal function [see Warnings and Precautions (5.6)]. • When these drugs are administered concomitantly, patients should be adequately hydrated. Assess renal function at the beginning of the concomitant treatment and periodically thereafter.
Diuretics
Clinical Impact: | Clinical studies, as well as post-marketing observations, showed that NSAIDs reduced the natriuretic effect of loop diuretics (e.g., furosemide) and thiazide diuretics in some patients. This effect has been attributed to the NSAID inhibition of renal prostaglandin synthesis.
Intervention: | During concomitant use of Piroxicam Capsules with diuretics, observe patients for signs of worsening renal function, in addition to assuring diuretic efficacy including antihypertensive effects [see Warnings and Precautions (5.6)].
Digoxin
Clinical Impact: | The concomitant use of piroxicam with digoxin has been reported to increase the serum concentration and prolong the half-life of digoxin.
Intervention: | During concomitant use of Piroxicam Capsules and digoxin, monitor serum digoxin levels.
Lithium
Clinical Impact: | NSAIDs have produced elevations in plasma lithium levels and reductions in renal lithium clearance. The mean minimum lithium concentration increased 15%, and the renal clearance decreased by approximately 20%. This effect has been attributed to NSAID inhibition of renal prostaglandin synthesis.
Intervention: | During concomitant use of Piroxicam Capsules and lithium, monitor patients for signs of lithium toxicity.
Methotrexate
Clinical Impact: | Concomitant use of NSAIDs and methotrexate may increase the risk for methotrexate toxicity (e.g., neutropenia, thrombocytopenia, renal dysfunction).
Intervention: | During concomitant use of Piroxicam Capsules and methotrexate, monitor patients for methotrexate toxicity.
Cyclosporine
Clinical Impact: | Concomitant use of Piroxicam Capsules and cyclosporine may increase cyclosporine's nephrotoxicity.
Intervention: | During concomitant use of Piroxicam Capsules and cyclosporine, monitor patients for signs of worsening renal function.
NSAIDs and Salicylates
Clinical Impact: | Concomitant use of piroxicam with other NSAIDs or salicylates (e.g., diflunisal, salsalate) increases the risk of GI toxicity, with little or no increase in efficacy [see Warnings and Precautions (5.2)].
Intervention: | The concomitant use of piroxicam with other NSAIDs or salicylates is not recommended.
Pemetrexed
Clinical Impact: | Concomitant use of Piroxicam Capsules and pemetrexed may increase the risk of pemetrexed-associated myelosuppression, renal, and GI toxicity (see the pemetrexed prescribing information).
Intervention: | During concomitant use of Piroxicam Capsules and pemetrexed, in patients with renal impairment whose creatinine clearance ranges from 45 to 79 mL/min, monitor for myelosuppression, renal and GI toxicity. NSAIDs with short elimination half-lives (e.g., diclofenac, indomethacin) should be avoided for a period of two days before, the day of, and two days following administration of pemetrexed. In the absence of data regarding potential interaction between pemetrexed and NSAIDs with longer half-lives (e.g., meloxicam, nabumetone), patients taking these NSAIDs should interrupt dosing for at least five days before, the day of, and two days following pemetrexed administration.
Highly Protein Bound Drugs
Clinical Impact: | Piroxicam Capsules are highly protein bound and, therefore, might be expected to displace other protein bound drugs.
Intervention: | Physicians should closely monitor patients for a change in dosage requirements when administering Piroxicam Capsules to patients on other highly protein bound drugs.
Corticosteroids
Clinical Impact: | Concomitant use of corticosteroids with Piroxicam Capsules may increase the risk of GI ulceration or bleeding.
Intervention: | Monitor patients with concomitant use of Piroxicam Capsules with corticosteroids for signs of bleeding [see Warnings and Precautions (5.2)].

8 USE IN SPECIFIC POPULATIONS

8.1 Pregnancy

Risk Summary

Use of NSAIDs, including Piroxicam Capsules, can cause premature closure of the fetal ductus arteriosus and fetal renal dysfunction leading to oligohydramnios and, in some cases, neonatal renal impairment. Because of these risks, limit dose and duration of Piroxicam Capsules use between about 20 and 30 weeks of gestation, and avoid Piroxicam Capsules use at about 30 weeks of gestation and later in pregnancy (see Clinical Considerations, Data).

Premature Closure of Fetal Ductus Arteriosus

Use of NSAIDs, including Piroxicam Capsules, at about 30 weeks gestation or later in pregnancy increases the risk of premature closure of the fetal ductus arteriosus.

Oligohydramnios/Neonatal Renal Impairment

Use of NSAIDs at about 20 weeks gestation or later in pregnancy has been associated with cases of fetal renal dysfunction leading to oligohydramnios, and in some cases, neonatal renal impairment.

Data from observational studies regarding other potential embryofetal risks of NSAID use in women in the first or second trimesters of pregnancy are inconclusive. In animal reproduction studies in rats and rabbits, there was no evidence of teratogenicity at exposures up to 5 and 10 times the maximum recommended human dose (MRHD), respectively. In rat studies with piroxicam, fetotoxicity (postimplantation loss) was observed at exposures 2 times the MRHD, and delayed parturition and an increased incidence of stillbirth were noted at doses equivalent to the MRHD of piroxicam. Based on animal data, prostaglandins have been shown to have an important role in endometrial vascular permeability, blastocyst implantation, and decidualization. In animal studies, administration of prostaglandin synthesis inhibitors such as piroxicam, resulted in increased pre- and post-implantation loss. Prostaglandins also have been shown to have an important role in fetal kidney development. In published animal studies, prostaglandin synthesis inhibitors have been reported to impair kidney development when administered at clinically relevant doses.

The estimated background risk of major birth defects and miscarriage for the indicated population(s) is unknown. All pregnancies have a background risk of birth defect, loss, or other adverse outcomes. In the U.S. general population, the estimated background risk of major birth defects and miscarriage in clinically recognized pregnancies is 2% to 4% and 15% to 20%, respectively.

Clinical Considerations

Fetal/Neonatal Adverse Reactions

Premature Closure of Fetal Ductus Arteriosus:

Avoid use of NSAIDs in women at about 30 weeks gestation and later in pregnancy, because NSAIDs, including Piroxicam Capsules, can cause premature closure of the fetal ductus arteriosus (see Data).

Oligohydramnios/Neonatal Renal Impairment:

If an NSAID is necessary at about 20 weeks gestation or later in pregnancy, limit the use to the lowest effective dose and shortest duration possible. If Piroxicam Capsules treatment extends beyond 48 hours, consider monitoring with ultrasound for oligohydramnios. If oligohydramnios occurs, discontinue Piroxicam Capsules and follow up according to clinical practice (see Data).

Labor or Delivery

There are no studies on the effects of Piroxicam Capsules during labor or delivery. In animal studies, NSAIDS, including piroxicam inhibit prostaglandin synthesis, cause delayed parturition, and increase the incidence of stillbirth.

Data

Human Data

Premature Closure of Fetal Ductus Arteriosus:

Published literature reports that the use of NSAIDs at about 30 weeks of gestation and later in pregnancy may cause premature closure of the fetal ductus arteriosus.

Oligohydramnios/Neonatal Renal Impairment:

Published studies and postmarketing reports describe maternal NSAID use at about 20 weeks gestation or later in pregnancy associated with fetal renal dysfunction leading to oligohydramnios, and in some cases, neonatal renal impairment. These adverse outcomes are seen, on average, after days to weeks of treatment, although oligohydramnios has been infrequently reported as soon as 48 hours after NSAID initiation. In many cases, but not all, the decrease in amniotic fluid was transient and reversible with cessation of the drug. There have been a limited number of case reports of maternal NSAID use and neonatal renal dysfunction without oligohydramnios, some of which were irreversible. Some cases of neonatal renal dysfunction required treatment with invasive procedures, such as exchange transfusion or dialysis.

Methodological limitations of these postmarketing studies and reports include lack of a control group; limited information regarding dose, duration, and timing of drug exposure; and concomitant use of other medications. These limitations preclude establishing a reliable estimate of the risk of adverse fetal and neonatal outcomes with maternal NSAID use. Because the published safety data on neonatal outcomes involved mostly preterm infants, the generalizability of certain reported risks to the full-term infant exposed to NSAIDs through maternal use is uncertain.

Animal Data

Pregnant rats administered piroxicam at 2, 5, or 10 mg/kg/day during the period of organogenesis (Gestation Days 6 to 15) demonstrated increased post-implantation losses with 5 and 10 mg/kg/day of piroxicam (equivalent to 2 and 5 times the MRHD, of 20 mg respectively, based on a mg/m^2body surface area [BSA]). There were no drug-related developmental abnormalities noted in offspring. Gastrointestinal tract toxicity was increased in pregnant rats in the last trimester of pregnancy compared to non-pregnant rats or rats in earlier trimesters of pregnancy. Pregnant rabbits administered piroxicam at 2, 5, or 10 mg/kg/day during the period of organogenesis (Gestation Days 7 to 18) demonstrated no drug-related developmental abnormalities in offspring (up to 10 times the MRHD based on a mg/m^2BSA).

In a pre- and post-natal development study in which pregnant rats were administered piroxicam at 2, 5, or 10 mg/kg/day on Gestation Day 15 through delivery and weaning of offspring, reduced weight gain and death were observed in dams at 10 mg/kg/day (5 times the MRHD based on a mg/m^2BSA) starting on Gestation Day 20. Treated dams revealed peritonitis, adhesions, gastric bleeding, hemorrhagic enteritis and dead fetuses in utero. Parturition was delayed and there was an increased incidence of stillbirth in all piroxicam-treated groups (at doses equivalent to the MRHD). Postnatal development could not be reliably assessed due to the absence of maternal care secondary to severe maternal toxicity.

8.2 Lactation

Risk Summary

Limited data from 2 published reports that included a total of 6 breastfeeding women and 2 infants showed piroxicam is excreted in human milk at approximately 1% to 3% of the maternal concentration. No accumulation of piroxicam occurred in milk relative to that in maternal plasma during treatment. The developmental and health benefits of breastfeeding should be considered along with the mother's clinical need for Piroxicam Capsules and any potential adverse effects on the breastfed infant from the Piroxicam Capsules or from the underlying maternal condition.

8.3 Females and Males of Reproductive Potential

Infertility

Females

Based on the mechanism of action, the use of prostaglandin-mediated NSAIDs, including Piroxicam Capsules, may delay or prevent rupture of ovarian follicles, which has been associated with reversible infertility in some women. Published animal studies have shown that administration of prostaglandin synthesis inhibitors has the potential to disrupt prostaglandin-mediated follicular rupture required for ovulation. Small studies in women treated with NSAIDs have also shown a reversible delay in ovulation. Consider withdrawal of NSAIDs, including Piroxicam Capsules, in women who have difficulties conceiving or who are undergoing investigation of infertility.

8.4 Pediatric Use

Piroxicam Capsules has not been investigated in pediatric patients. The safety and effectiveness of Piroxicam Capsules have not been established.

8.5 Geriatric Use

Elderly patients, compared to younger patients, are at greater risk for NSAID-associated serious cardiovascular, gastrointestinal, and/or renal adverse reactions. If the anticipated benefit for the elderly patient outweighs these potential risks, start dosing at the low end of the dosing range, and monitor patients for adverse effects [see Warnings and Precautions (5.1, 5.2, 5.3, 5.6, 5.14)].

10 OVERDOSAGE

Symptoms following acute NSAID overdoses have been typically limited to lethargy, drowsiness, nausea, vomiting, and epigastric pain, which are generally reversible with supportive care. Gastrointestinal bleeding has occurred. Hypertension, acute renal failure, respiratory depression, and coma have occurred, but were rare [see Warnings and Precautions (5.1, 5.2, 5.4, 5.6)].

Manage patients with symptomatic and supportive care following an acute NSAID overdose. There are no specific antidotes. It is advisable to contact a poison control center (1-800-222-1222) to determine the latest recommendations because strategies for the management of overdose are continually evolving.

If gastric decontamination may be potentially beneficial to the patient, e.g., short time since ingestion or a large overdosage (5 to 10 times the recommended dosage), consider emesis and/or activated charcoal (60 grams to 100 grams in adults, 1 gram to 2 grams per kg of body weight in pediatric patients) and/or an osmotic cathartic in symptomatic patients.

The long plasma half-life of piroxicam should be considered when treating an overdose with piroxicam. Forced diuresis, alkalinization of urine, hemodialysis, or hemoperfusion may not be useful due to high protein binding.

11 DESCRIPTION

Piroxicam Capsules USP is a nonsteroidal anti-inflammatory drug, available as maroon and blue #10 mg capsules and maroon #20 mg capsules for oral administration. The chemical name is 4-hydroxyl-2-methyl- N-2 pyridinyl-2 H-1,2,-benzothiazine-3-carboxamide 1,1-dioxide. The molecular weight is 331.35. Its molecular formula is C15H13N3O4S, and it has the following chemical structure.

Piroxicam, USP occurs as a white or slightly yellow crystalline powder, soluble in methylene chloride, slightly soluble in ethanol and practically insoluble in water. It exhibits a weakly acidic 4-hydroxy proton (pKa 5.1) and a weakly basic pyridyl nitrogen (pKa 1.8).

In addition to the active ingredient, each capsule contains corn starch, lactose monohydrate, magnesium stearate and sodium lauryl sulfate. The 10mg capsule shell contains FD&C Blue 1, FD&C Red 3, titanium dioxide, gelatin and water. The 20mg capsule shell contains FD&C Blue 1, FD&C Red 3, titanium dioxide, gelatin and water. The imprinting ink contains shellac, titanium dioxide and trace amount (less than 1 ppb) of potassium salts of potassium hydroxides.

12 CLINICAL PHARMACOLOGY

12.1 Mechanism of Action

Piroxicam has analgesic, anti-inflammatory, and antipyretic properties.

The mechanism of action of Piroxicam Capsules, like that of other NSAIDs, is not completely understood but involves inhibition of cyclooxygenase (COX-1 and COX-2).

Piroxicam is a potent inhibitor of prostaglandin (PG) synthesis in vitro. Piroxicam concentrations reached during therapy have produced in vivo effects. Prostaglandins sensitize afferent nerves and potentiate the action of bradykinin in inducing pain in animal models. Prostaglandins are mediators of inflammation. Because piroxicam is an inhibitor of prostaglandin synthesis, its mode of action may be due to a decrease of prostaglandins in peripheral tissues.

12.3 Pharmacokinetics

General Pharmacokinetic Characteristics

The pharmacokinetics of piroxicam have been characterized in healthy subjects, special populations and patients. The pharmacokinetics of piroxicam are linear. Proportional increase in exposure is observed with increasing doses. The prolonged half-life (50 hours) results in the maintenance of relatively stable plasma concentrations throughout the day on once daily doses and significant accumulation upon multiple dosing. Most patients approximate steady state plasma levels within 7 to 12 days. Higher levels, which approximate steady state at two to three weeks, have been observed in patients in whom longer plasma half-lives of piroxicam occurred.

Absorption

Piroxicam is well absorbed following oral administration. Drug plasma concentrations are proportional for 10 mg and 20 mg doses and generally peak within three to five hours after administration. A single 20 mg dose generally produces peak piroxicam plasma levels of 1.5 mcg/mL to 2 mcg/mL, while maximum drug plasma concentrations, after repeated daily administration of 20 mg piroxicam, usually stabilize at 3 mcg/mL to 8 mcg/mL.

With food there is a slight delay in the rate but not the extent of absorption following oral administration. The concomitant administration of antacids (aluminum hydroxide or aluminum hydroxide with magnesium hydroxide) have been shown to have no effect on the plasma levels of orally administered piroxicam.

Distribution

The apparent volume of distribution of piroxicam is approximately 0.14 L/kg. Ninety nine percent of plasma piroxicam is bound to plasma proteins. Piroxicam is excreted into human milk. The presence in breast milk has been determined during initial and long term conditions (52 days). Piroxicam appeared in breast milk at approximately 1% to 3% of the maternal concentration. No accumulation of piroxicam occurred in milk relative to that in plasma during treatment.

Elimination

Metabolism

Metabolism of piroxicam occurs by hydroxylation at the 5 position of the pyridyl side chain and conjugation of this product; by cyclodehydration; and by a sequence of reactions involving hydrolysis of the amide linkage, decarboxylation, ring contraction, and N-demethylation .In vitro studies indicate cytochrome P4502C9 (CYP2C9) as the main enzyme involved in the formation to the 5′-hydroxy-piroxicam, the major metabolite [see Clinical Pharmacology (12.5)].The biotransformation products of piroxicam metabolism are reported to not have any anti-inflammatory activity.

Higher systemic exposure of piroxicam has been noted in subjects with CYP2C9 polymorphisms compared to normal metabolizer type subjects [see Clinical Pharmacology (12.5)].

Excretion

Piroxicam and its biotransformation products are excreted in urine and feces, with about twice as much appearing in the urine as in the feces. Approximately 5% of a Piroxicam Capsules dose is excreted unchanged. The plasma half-life (t½) for piroxicam is approximately 50 hours.

Specific Populations

Pediatric

Piroxicam has not been investigated in pediatric patients.

Race

Pharmacokinetic differences due to race have not been identified.

Hepatic Impairment

The effects of hepatic disease on piroxicam pharmacokinetics have not been established. However, a substantial portion of piroxicam elimination occurs by hepatic metabolism. Consequently, patients with hepatic disease may require reduced doses of piroxicam as compared to patients with normal hepatic function.

Renal Impairment

Piroxicam pharmacokinetics have been investigated in patients with renal insufficiency. Studies indicate patients with mild to moderate renal impairment may not require dosing adjustments. However, the pharmacokinetic properties of piroxicam in patients with severe renal insufficiency or those receiving hemodialysis are not known.

Drug Interaction Studies

Antacids

Concomitant administration of antacids had no effect on piroxicam plasma levels.

Aspirin

When piroxicam was administered with aspirin, its protein binding was reduced, although the clearance of free Piroxicam Capsules was not altered. Plasma levels of piroxicam were decreased to approximately 80% of their normal values when Piroxicam Capsules was administered (20 mg/day) in conjunction with aspirin (3900 mg/day). The clinical significance of this interaction is not known [see Drug Interactions (7)].

12.5 Pharmacogenomics

CYP2C9 activity is reduced in individuals with genetic polymorphisms, such as the CYP2C9*2 and CYP2C9*3 polymorphisms. Limited data from two published reports showed that subjects with heterozygous CYP2C9*1/*2 (n=9), heterozygous CYP2C9*1/*3 (n=9), and homozygous CYP2C9*3/*3 (n=1) genotypes showed 1.7-, 1.7-, and 5.3-fold higher piroxicam systemic levels, respectively, than the subjects with CYP2C9*1/*1 (n=17, normal metabolizer genotype) following administration of a single oral dose. The mean elimination half-life values of piroxicam for subjects with CYP2C9*1/*3 (n=9) and CYP2C9*3/*3 (n=1) genotypes were 1.7- and 8.8-fold higher than subjects with CYP2C9*1/*1 (n=17). It is estimated that the frequency of the homozygous*3/*3 genotype is 0% to 1% in the population at large; however, frequencies as high as 5.7% have been reported in certain ethnic groups.

Poor Metabolizers of CYP2C9 Substrates: In patients who are known or suspected to be poor CYP2C9 metabolizers based on genotype or previous history/experience with other CYP2C9 substrates (such as warfarin and phenytoin) consider dose reduction as they may have abnormally high plasma levels due to reduced metabolic clearance.

13 NONCLINICAL TOXICOLOGY

13.1 Carcinogenesis, Mutagenesis, Impairment of Fertility

Carcinogenesis

Long-term animal studies have not been conducted to characterize the carcinogenic potential of piroxicam.

Mutagenesis

Piroxicam was not mutagenic in an Ames bacterial reverse mutation assay, or in a dominant lethal mutation assay in mice, and was not clastogenic in an in vivo chromosome aberration assay in mice.

Impairment of Fertility

Reproductive studies in which rats were administered piroxicam at doses of 2, 5, or 10 mg/kg/day (up to 5 times the MRHD of 20 mg based on mg/m^2body surface area [BSA]) revealed no impairment of male or female fertility.

14 CLINICAL STUDIES

In controlled clinical trials, the effectiveness of Piroxicam Capsules has been established for both acute exacerbations and long term management of rheumatoid arthritis and osteoarthritis.

The therapeutic effects of Piroxicam Capsules are evident early in the treatment of both diseases with a progressive increase in response over several (8–12) weeks. Efficacy is seen in terms of pain relief and, when present, subsidence of inflammation.

Doses of 20 mg/day Piroxicam Capsules display a therapeutic effect comparable to therapeutic doses of aspirin, with a lower incidence of minor gastrointestinal effects and tinnitus.

Piroxicam Capsules has been administered concomitantly with fixed doses of gold and corticosteroids. The existence of a "steroid sparing" effect has not been adequately studied to date.

16 HOW SUPPLIED/STORAGE AND HANDLING

Piroxicam Capsules USP, 10mg are maroon opaque cap and blue opaque body imprinted with 'P10' on body, supplied as

NDC Number Size

42291-953-01 Bottle of 100

Piroxicam Capsules USP, 20mg are maroon opaque cap and maroon opaque body imprinted with "P20" on body, supplied as

NDC Number Size

42291-954-01 Bottle of 100

42291-954-50 Bottle of 500

Storage

Store at room temperature 20°C to 25°C (68°F to 77°F); excursions permitted between 15°C to 30°C (59°F to 86°F) [see USP Controlled Room Temperature].

17 PATIENT COUNSELING INFORMATION

Advise the patient to read the FDA-approved patient labeling (Medication Guide) that accompanies each prescription dispensed. Inform patients, families, or their caregivers of the following information before initiating therapy with Piroxicam Capsules and periodically during the course of ongoing therapy.

Cardiovascular Thrombotic Events

Advise patients to be alert for the symptoms of cardiovascular thrombotic events, including chest pain, shortness of breath, weakness, or slurring of speech, and to report any of these symptoms to their health care provider immediately [see Warnings and Precautions (5.1)].

Gastrointestinal Bleeding, Ulceration, and Perforation

Advise patients to report symptoms of ulcerations and bleeding, including epigastric pain, dyspepsia, melena, and hematemesis to their health care provider. In the setting of concomitant use of low-dose aspirin for cardiac prophylaxis, inform patients of the increased risk for and the signs and symptoms of GI bleeding [see Warnings and Precautions (5.2)].

Hepatotoxicity

Inform patients of the warning signs and symptoms of hepatotoxicity (e.g., nausea, fatigue, lethargy, pruritus, diarrhea, jaundice, right upper quadrant tenderness, and "flu-like" symptoms). If these occur, instruct patients to stop Piroxicam Capsules and seek immediate medical therapy [see Warnings and Precautions (5.3)].

Heart Failure and Edema

Advise patients to be alert for the symptoms of congestive heart failure including shortness of breath, unexplained weight gain, or edema and to contact their healthcare provider if such symptoms occur [see Warnings and Precautions (5.5)].

Anaphylactic Reactions

Inform patients of the signs of an anaphylactic reaction (e.g., difficulty breathing, swelling of the face or throat). Instruct patients to seek immediate emergency help if these occur [see Contraindications (4) and Warnings and Precautions (5.7)].

Serious Skin Reactions, including DRESS

Advise patients to stop taking Piroxicam Capsules immediately if they develop any type of rash or fever and to contact their healthcare provider as soon as possible [see Warnings and Precautions (5.9, 5.10)].

Female Fertility

Advise females of reproductive potential who desire pregnancy that NSAIDs, including Piroxicam Capsules, may be associated with a reversible delay in ovulation [ see Use in Specific Populations (8.3)].

Fetal Toxicity

Inform pregnant women to avoid use of Piroxicam Capsules and other NSAIDs starting at 30 weeks gestation because of the risk of the premature closing of the fetal ductus arteriosus. If treatment with Piroxicam Capsules is needed for a pregnant woman between about 20 to 30 weeks gestation, advise her that she may need to be monitored for oligohydramnios, if treatment continues for longer than 48 hours [see Warnings and Precautions (5.11) and Use in Specific Populations (8.1)].

Avoid Concomitant Use of NSAIDs

Inform patients that the concomitant use of Piroxicam Capsules with other NSAIDs or salicylates (e.g., diflunisal, salsalate) is not recommended due to the increased risk of gastrointestinal toxicity, and little or no increase in efficacy [see Warnings and Precautions (5.2) and Drug Interactions (7)].Alert patients that NSAIDs may be present in "over the counter" medications for treatment of colds, fever, or insomnia.

Use of NSAIDS and Low-Dose Aspirin

Inform patients not to use low-dose aspirin concomitantly with Piroxicam Capsules until they talk to their healthcare provider [see Drug Interactions (7)].

Manufactured for:
AvKARE

Pulaski, TN 38478

Mfg. Rev. 12/22

Mfg. 07/24 (P)

Medication Guide available at: www.avkare.com

Medication Guide for Nonsteroidal Anti-inflammatory Drugs (NSAIDs)

What is the most important information I should know about medicines called Nonsteroidal Anti-inflammatory Drugs (NSAIDs)?
NSAIDs can cause serious side effects, including:
• Increased risk of a heart attack or stroke that can lead to death.This risk may happen early in treatment and may increase:
o with increasing doses of NSAIDs
o with longer use of NSAIDs
Do not take NSAIDs right before or after a heart surgery called a "coronary artery bypass graft (CABG)."
Avoid taking NSAIDs after a recent heart attack, unless your healthcare provider tells you to. You may have an increased risk of another heart attack if you take NSAIDs after a recent heart attack.

- Increased risk of bleeding, ulcers, and tears (perforation) of the esophagus (tube leading from the mouth to the stomach), stomach and intestines:
  - anytime during use
  - without warning symptoms
  - that may cause death

- The risk of getting an ulcer or bleeding increases with:

- past history of stomach ulcers, or stomach or intestinal bleeding with use of NSAIDs
- taking medicines called "corticosteroids," "antiplatelet drugs," "anticoagulants," "SSRIs" or "SNRIs"

- increasing doses of NSAIDs
- longer use of NSAIDs
- smoking
- drinking alcohol

- older age
- poor health
- advanced liver disease
- bleeding problems

- NSAIDs should only be used:
  - exactly as prescribed
  - at the lowest dose possible for your treatment
  - for the shortest time needed

What are NSAIDs?
NSAIDs are used to treat pain and redness, swelling, and heat (inflammation) from medical conditions such as different types of arthritis, menstrual cramps, and other types of short-term pain.

Who should not take NSAIDs?
Do not take NSAIDs:
• if you have had an asthma attack, hives, or other allergic reaction with aspirin or any other NSAIDs.
• right before or after heart bypass surgery.

Before taking NSAIDS, tell your healthcare provider about all of your medical conditions, including if you:
• have liver or kidney problems
• have high blood pressure
• have asthma
• are pregnant or plan to become pregnant. Taking NSAIDs at about 20 weeks of pregnancy or later may harm your unborn baby. If you need to take NSAIDs for more than 2 days when you are between 20 and 30 weeks of pregnancy, your healthcare provider may need to monitor the amount of fluid in your womb around your baby. You should not take NSAIDs after about 30 weeks of pregnancy.
• are breastfeeding or plan to breast feed
Tell your healthcare provider about all of the medicines you take, including prescription or over-the-counter medicines, vitamins or herbal supplements.NSAIDs and some other medicines can interact with each other and cause serious side effects. Do not start taking any new medicine without talking to your healthcare provider first.

What are the possible side effects of NSAIDs?
NSAIDs can cause serious side effects, including:
See "What is the most important information I should know about medicines called Nonsteroidal Anti-inflammatory Drugs (NSAIDs)?"
• new or worse high blood pressure
• heart failure
• liver problems including liver failure
• kidney problems including kidney failure
• low red blood cells (anemia)
• life-threatening skin reactions
• life-threatening allergic reactions
• Other side effects of NSAIDs include:stomach pain, constipation, diarrhea, gas, heartburn, nausea, vomiting, and dizziness.
Get emergency help right away if you get any of the following symptoms:
• shortness of breath or trouble breathing • slurred speech
• chest pain • swelling of the face or throat
• weakness in one part or side of your body
Stop taking your NSAID and call your healthcare provider right away if you get any of the following symptoms:
• nausea

• more tired or weaker than usual

• vomit blood

• diarrhea

• there is blood in your bowel movement or it is black and sticky like tar

• itching

• unusual weight gain

• your skin or eyes look yellow

• skin rash or blisters with fever

• indigestion or stomach pain

• swelling of the arms, legs, hands and feet

• flu-like symptoms

If you take too much of your NSAID, call your healthcare provider or get medical help right away.
These are not all the possible side effects of NSAIDs. For more information, ask your healthcare provider or pharmacist about NSAIDs.
Call your doctor for medical advice about side effects. You may report side effects to FDA at 1-800-FDA-1088 or AvKARE at 1-855-361-3993.

Other information about NSAIDs
• Aspirin is an NSAID but it does not increase the chance of a heart attack. Aspirin can cause bleeding in the brain, stomach, and intestines. Aspirin can also cause ulcers in the stomach and intestines.
• Some NSAIDs are sold in lower doses without a prescription (over-the-counter). Talk to your healthcare provider before using over-the-counter NSAIDs for more than 10 days.

General information about the safe and effective use of NSAIDs
Medicines are sometimes prescribed for purposes other than those listed in a Medication Guide. Do not use NSAIDs for a condition for which it was not prescribed. Do not give NSAIDs to other people, even if they have the same symptoms that you have. It may harm them.
If you would like more information about NSAIDs, talk with your healthcare provider. You can ask your pharmacist or healthcare provider for information about NSAIDs that is written for health professionals.

Manufactured for:
AvKARE

Pulaski, TN 38478

Mfg. Rev. 12/22

Mfg. 07/24 (P)

This Medication Guide has been approved by the U.S. Food and Drug Administration.